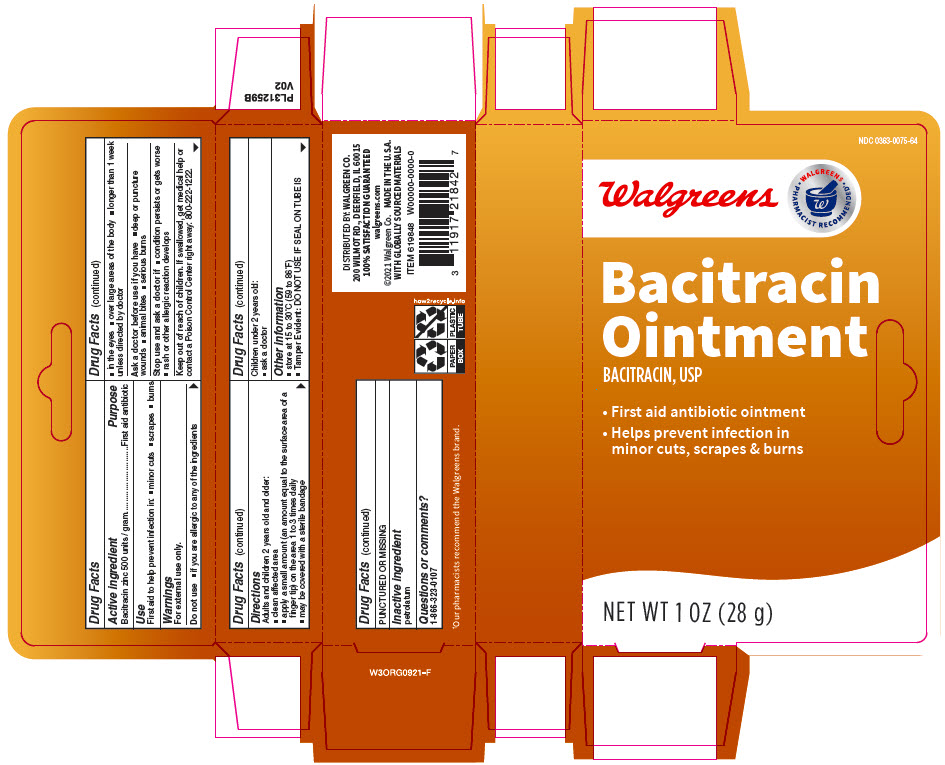 DRUG LABEL: Bacitracin
NDC: 0363-0075 | Form: OINTMENT
Manufacturer: Walgreen Company
Category: otc | Type: HUMAN OTC DRUG LABEL
Date: 20220120

ACTIVE INGREDIENTS: BACITRACIN 500 [USP'U]/1 g
INACTIVE INGREDIENTS: LIGHT MINERAL OIL; PETROLATUM

Walgreen Co. Bacitracin Ointment

Drug Facts

Active ingredient

Bacitracin zinc 500 units / gram

Purpose

First aid antibiotic

Use

First aid to help prevent infection in:

- minor cuts
- scrapes
- burns

Warnings

For external use only.

Do not use

- if you are allergic to any of the ingredients
- in the eyes
- over large areas of the body
- longer than 1 week unless directed by doctor

Ask a doctor before use if you have

- deep or puncture wounds
- animal bites
- serious burns

Stop use and ask a doctor if

- condition persists or gets worse
- rash or other allergic reaction develops

Keep out of reach of children. If swallowed, get medical help or contact a Poison Control Center right away: 800-222-1222.

Directions

Adults and children 2 years old and older:

- clean affected area
- apply a small amount (an amount equal to the surface area of a finger tip) on the area 1 to 3 times daily
- may be covered with a sterile bandage

Children under 2 years old:

- ask a doctor

Other information

- store at 15 to 30°C (59 to 86°F)
- Tamper Evident: DO NOT USE IF SEAL ON TUBE IS PUNCTURED OR MISSING

Inactive ingredient

petrolatum

Questions or comments?

866-323-0107

DISTRIBUTED BY: WALGREEN CO.
200 WILMOT RD., DEERFIELD, IL 60015

PRINCIPAL DISPLAY PANEL - 28 g Tube Carton

NDC 0363-0075-64

Walgreens

• WALGREENS •
PHARMACIST RECOMMENDED†

Bacitracin
Ointment
BACITRACIN, USP

- First aid antibiotic ointment
- Helps prevent infection in
  minor cuts, scrapes & burns

NET WT 1 OZ (28 g)